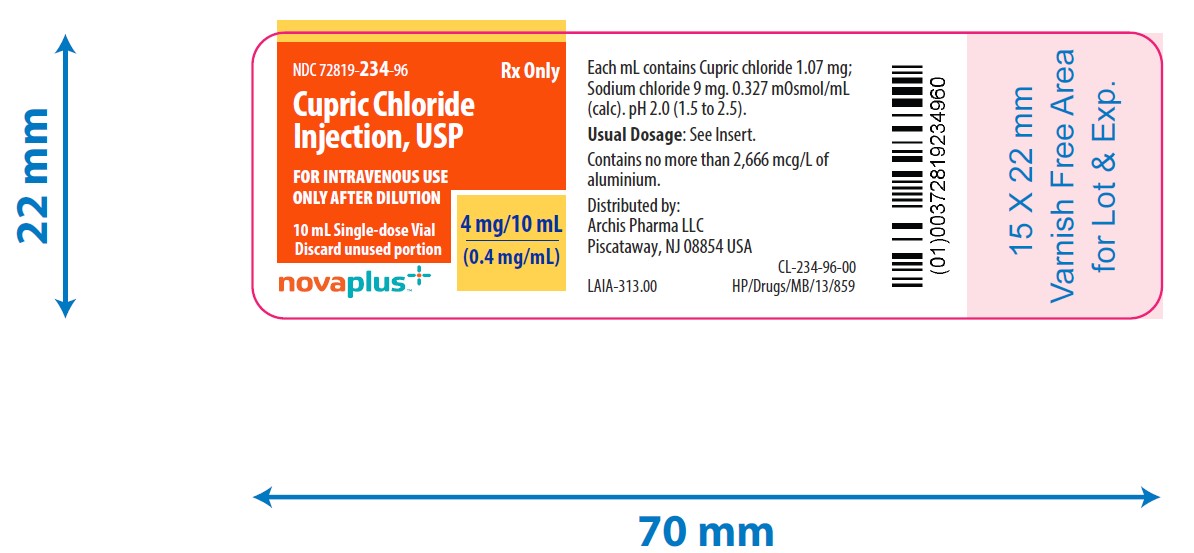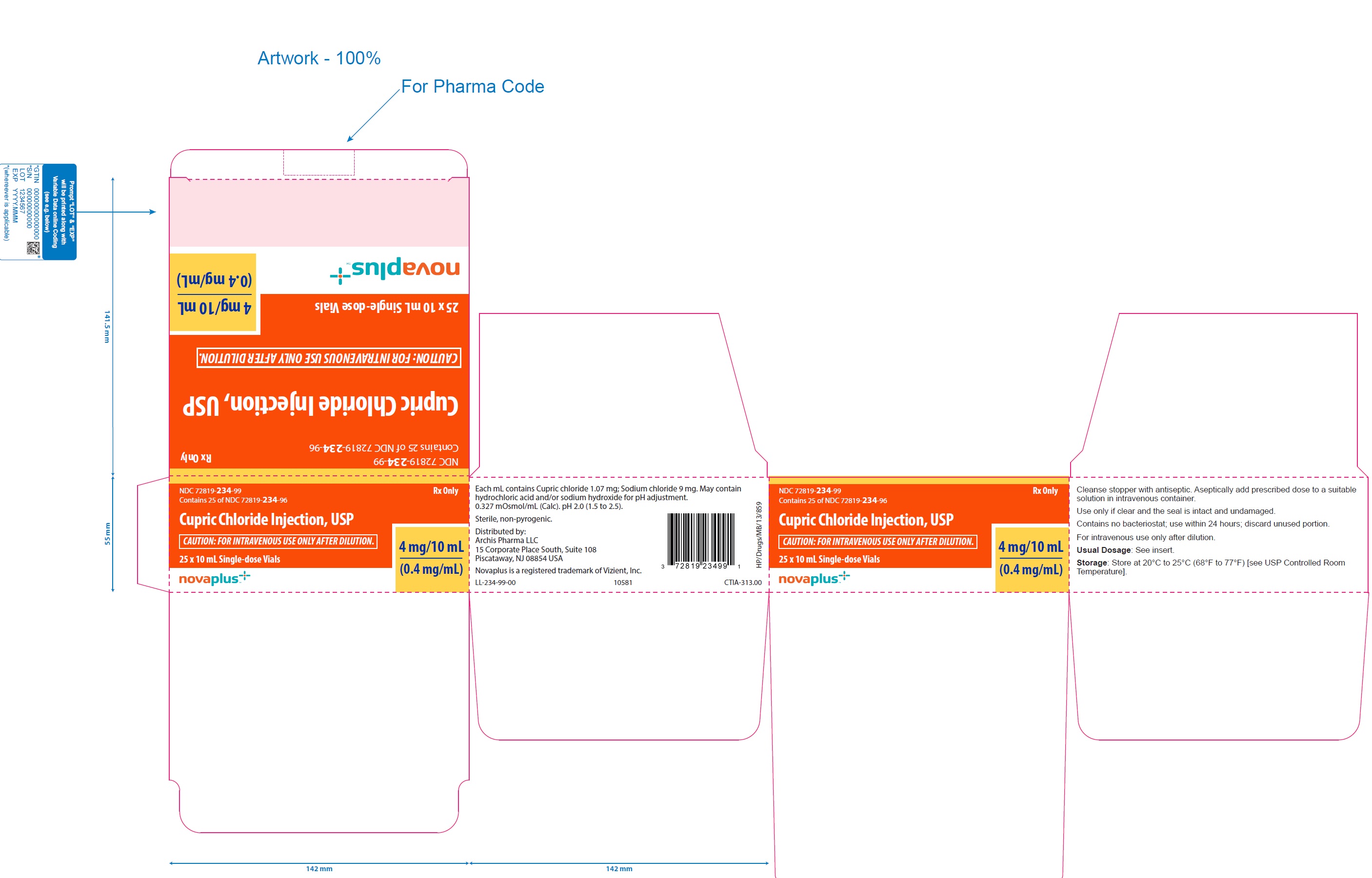 DRUG LABEL: CUPRIC CHLORIDE
NDC: 72819-234 | Form: INJECTION, SOLUTION
Manufacturer: Archis Pharma LLC
Category: prescription | Type: HUMAN PRESCRIPTION DRUG LABEL
Date: 20241016

ACTIVE INGREDIENTS: CUPRIC CHLORIDE 0.4 mg/1 mL
INACTIVE INGREDIENTS: SODIUM CHLORIDE 9 mg/1 mL; HYDROCHLORIC ACID; SODIUM HYDROXIDE

Cupric Chloride Injection, USP 0.4 mg/mL
Novaplus
FOR I.V. USE ONLY AFTER DILUTION
Glass Vial
Rx only

DESCRIPTION

Cupric Chloride Injection, USP is a sterile, nonpyrogenic solution intended for use as an additive to intravenous solutions for total parenteral nutrition (TPN). Each mL of solution contains 1.07 mg cupric chloride, dihydrate and 9 mg sodium chloride.

The solution contains no bacteriostat, antimicrobial agent or added buffer. The pH is 2.0 (1.5 to 2.5); product may contain hydrochloric acid and/or sodium hydroxide for pH adjustment. The osmolarity is 0.327 mOsmol/mL (calc.).

Cupric chloride, USP is chemically designated cupric chloride, dihydrate (CuCl2•2H2O), a crystalline compound freely soluble in water.

Sodium Chloride, USP is chemically designated NaCl, a white crystalline compound freely soluble in water.

CLINICAL PHARMACOLOGY

Copper is an essential nutrient which serves as a cofactor for serum ceruloplasmin, an oxidase necessary for proper formation of the iron carrier protein, transferrin. Copper also helps maintain normal rates of red and white blood cell formation.

Providing copper during TPN helps prevent development of the following deficiency symptoms: Leukopenia, neutropenia, anemia, depressed ceruloplasmin levels, impaired transferrin formation, secondary iron deficiency and osteoporosis.

Normal serum copper values range from 80 to 163 mcg/dl (mean, approximately 110 mcg/dl). The serum copper level at which deficiency symptoms appear is not precisely defined. A serum value of 9 mcg copper/dl was reported for one TPN patient who received no copper. The daily turnover of copper through ceruloplasmin is approximately 0.5 mg. Excretion of copper is through the bile (80%), directly through the intestinal wall (16%) and in urine (4%).

INDICATIONS AND USAGE

Cupric chloride injection, USP is indicated for use as a supplement to intravenous solutions given for TPN. Administration helps to maintain copper serum levels and to prevent depletion of endogenous stores and subsequent deficiency symptoms.

CONTRAINDICATIONS

None known.

WARNINGS

Direct intramuscular or intravenous injection of cupric chloride injection is contraindicated, as the acidic pH of the solution (2) may cause considerable tissue irritation.

Liver and/or biliary tract dysfunction may require omission or reduction of copper and manganese doses because these elements are primarily eliminated in the bile.

WARNING:This product contains aluminum that may be toxic. Aluminum may reach toxic levels with prolonged parenteral administration if kidney function is impaired.

Premature neonates are particularly at risk because their kidneys are immature, and they require large amounts of calcium and phosphate solutions, which contain aluminum.

Research indicates that patients with impaired kidney function, including premature neonates, who receive parenteral levels of aluminum at greater than 4 to 5 mcg/kg/day accumulate aluminum at levels associated with central nervous system and bone toxicity. Tissue loading may occur at even lower rates of administration.

PRECAUTIONS

General
Do not use unless the solution is clear and the seal is intact.

Administration of zinc in the absence of copper may cause a decrease in serum copper levels.

Cupric chloride injection should only be used in conjunction with a pharmacy directed admixture program using aseptic technique in a laminar flow environment; it should be used promptly and in a single operation without any repeated penetrations. Solution contains no preservatives; discard unused portion immediately after admixture procedure is completed.

It is not recommended to administer copper to a patient with Wilson’s Disease, a genetic disease of copper metabolism.

Drug Interactions
Cupric ion may degrade ascorbic acid in total parenteral nutrition (TPN) solutions. In order to avoid this loss of ascorbate, multivitamin additives should be added to TPN solutions immediately prior to infusion. Alternatively, the multivitamin additive may be added to one container of TPN solution, followed by copper in a subsequent container.

Laboratory Tests
Twice monthly serum assays for copper and/or ceruloplasmin are suggested for monitoring copper concentrations in long-term TPN patients. As ceruloplasmin is a cuproenzyme, ceruloplasmin assays may be depressed secondary to copper deficiency.

Carcinogenesis, Mutagenesis, and Impairment of Fertility
Long-term animal studies to evaluate the carcinogenic potential of cupric chloride injection have not been performed, nor have studies been done to assess mutagenesis or impairment of fertility.

Nursing Mothers
It is not known whether this drug is excreted in human milk. Because many drugs are excreted in human milk, caution should be exercised when cupric chloride injection is administered to a nursing woman.

Pediatric Use

(See DOSAGE AND ADMINISTRATIONSection.) There are limited data in infants weighing less than 1500 grams.

Pregnancy
Animal reproduction studies have not been conducted with cupric chloride. It is also not known whether cupric chloride can cause fetal harm when administered to a pregnant woman or can affect reproductive capacity. Cupric chloride should be given to a pregnant woman only if clearly indicated.

Geriatric Use
An evaluation of current literature revealed no clinical experience identifying differences in response between elderly and younger patients. In general, dose selection for an elderly patient should be cautious, usually starting at the low end of the dosing range, reflecting the greater frequency of decreased hepatic, renal, or cardiac function, and of concomitant disease or other drug therapy.

ADVERSE REACTIONS

None known.

DRUG ABUSE AND DEPENDENCE

None known.

OVERDOSAGE

Copper toxicity can produce prostration, behavior change, diarrhea, progressive marasmus, hypotonia, photophobia and peripheral edema. Such symptoms have been reported with a serum copper level of 286 mcg/dl. Copper toxicity can also result in hemolysis and liver toxicity, including hepatic necrosis which may be fatal. D-penicillamine has been reported effective as an antidote.

DOSAGE AND ADMINISTRATION

Cupric Chloride Injection contains 0.4 mg copper/mL and is administered intravenously only after dilution. The additive should be diluted in a volume of fluid not less than 100 mL. For the adult receiving TPN, the suggested additive dosage is 0.5 to 1.5 mg copper/day (1.25 to 3.75 mL/day). For pediatric patients, the suggested additive dosage is 20 mcg copper/kg/day (0.05 mL/kg/day). Infants weighing less than 1500 gm may have increased requirements because of their low body reserves and increased requirements for growth.

Parenteral drug products should be inspected visually for particulate matter and discoloration prior to administration, whenever solution and container permit. (See PRECAUTIONS.)

HOW SUPPLIED

Cupric Chloride Injection, USP 0.4 mg/mL is supplied as follows:

NDC 72819-234-96 10 mL Single-dose glass vial

NDC 72819-234-99 Carton of 25 x 10 mL Single-dose glass vials.

Storage: Store at 20° to 25°C (68° to 77°F) [see USP Controlled Room Temperature].

Distributed by:
Archis Pharma LLC
15 Corporate Place South, Suite 108
Piscataway, NJ 08854 U.S.A

Novaplus is a registered trademark of Vizient, Inc.

Rev. 08/2024
PI-CUC-00-NP
LEIA-313.00
10582

Principal Display Panel Text for Container Label:

NDC 72819- 234-96

Cupric Chloride Injection, USP 4 mg/10 mL (0.4 mg/mL)

10 mL Single-dose Vials

Rx only

Principal Display Panel Text for Carton Label:

NDC 72819- 234-99

Cupric Chloride Injection, USP 4 mg/10 mL (0.4 mg/mL)

10 mL Single-dose vials in package of 25

Rx only